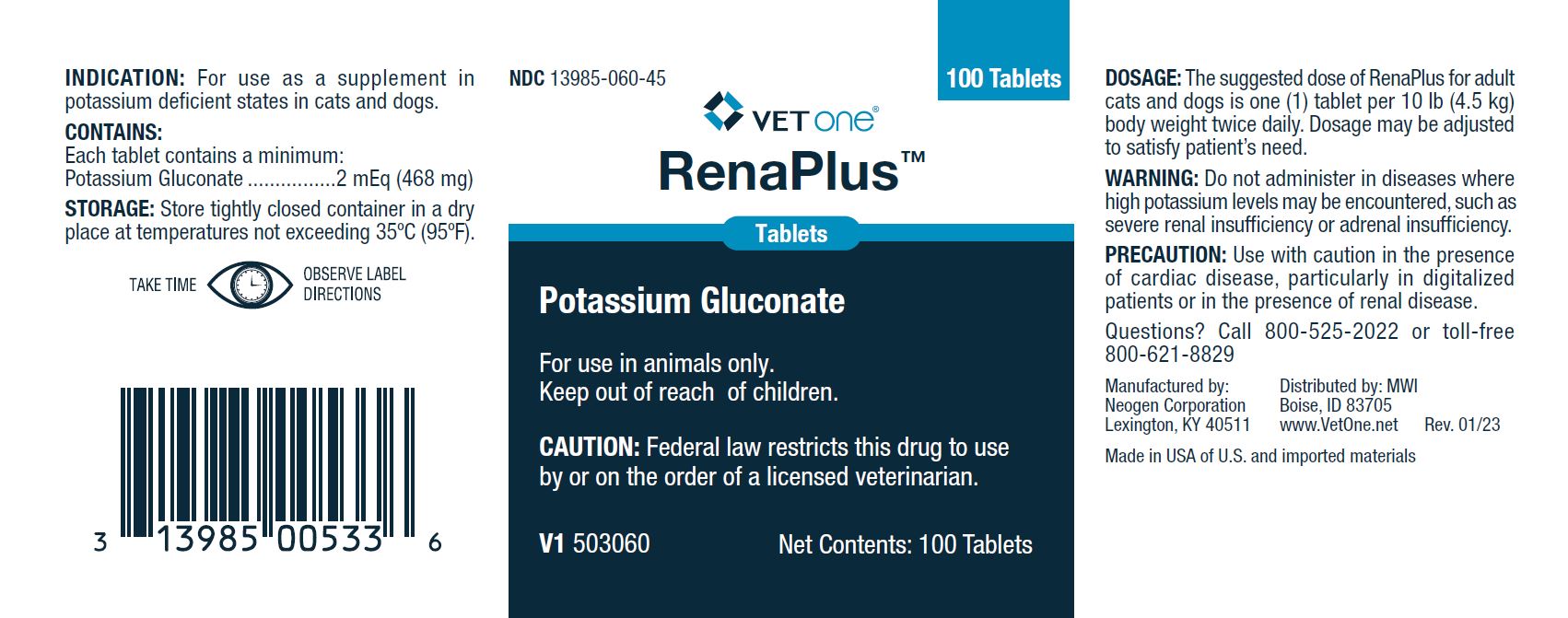 DRUG LABEL: RenaPlus
NDC: 13985-060 | Form: TABLET
Manufacturer: MWI/VetOne
Category: animal | Type: PRESCRIPTION ANIMAL DRUG LABEL
Date: 20240510

ACTIVE INGREDIENTS: POTASSIUM GLUCONATE 468 mg/1 1

DESCRIPTION

NDC 13985-060-45
VETone®

RenaPlus

Tablets

Potassium Gluconate

For use in animals only.

Keep out of reach of children.

CAUTION: Federal law restricts this drug to use by or on the order of a licensed veterinarian.

INDICATION:

For use as a supplement in potassium deficient states in cats and dogs.

CONTAINS:

Each tablet contains a minimum:

Potassium Gluconate........2 mEq (468 mg)

STORAGE:

Store tightly closed container in a dry place at temperatures not exceeding 35°C (95°F).

Distributed by: MWI

Boise, ID 83705

www.VetOne.net

Manufactured by:

Neogen Corporation

Lexington, KY 40511

Rev. 01/23

Made in USA of U.S. and imported materials

DOSAGE:

The suggested dose of RenaPlus for adult cats and dogs is one (1) tablet per 10 lb (4.5 kg) body weight twice daily. Dosage may be adjusted to satisfy patient's need.

WARNING:

Do not administer in diseases where high potassium levels may be encountered, such as severe renal insufficiency or adrenal insufficiency.

PRECAUTION:

Use with caution in the presence of cardiac disease, particularly in digitalized patients or in the presence of renal disease.

Questions? Call 800-525-2022 or toll-free 800-621-8829

DISPLAY PANEL - RENAPLUS TABLETS 100 Tablet Bottle

NDC 13985-060-45

VETone®

RenaPlus™

Tablets

Potassium Gluconate

For use in animals only.

Keep out of reach of children.

CAUTION: Federal law restricts this drug to use by or on the order of a licensed veterinarian.

V1 503060

Net Contents: 100 Tablets